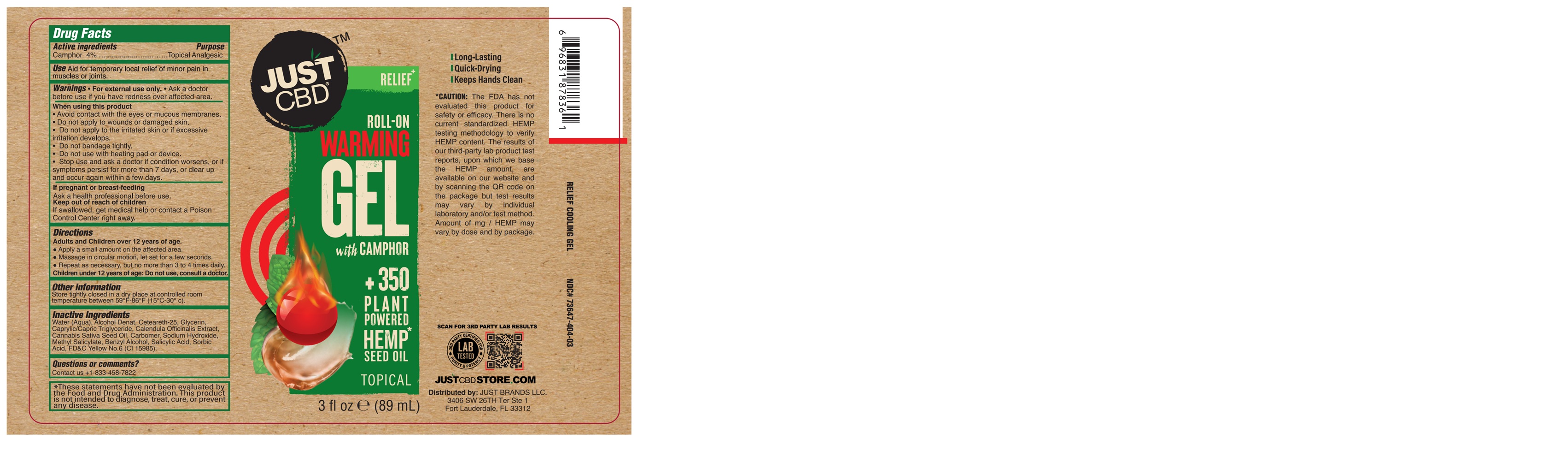 DRUG LABEL: JUST CBD ROLL-ON WARMING
NDC: 73647-404 | Form: GEL
Manufacturer: Just Brands LLC
Category: otc | Type: HUMAN OTC DRUG LABEL
Date: 20251205

ACTIVE INGREDIENTS: CAMPHOR (NATURAL) 4 g/100 mL
INACTIVE INGREDIENTS: WATER; CETEARETH-25; SALICYLIC ACID; FD&C YELLOW NO. 6; CARBOMER 940; CANNABIS SATIVA SEED OIL; CALENDULA OFFICINALIS FLOWER; BENZYL ALCOHOL; SORBIC ACID; SODIUM HYDROXIDE; METHYL SALICYLATE; ALCOHOL; MEDIUM-CHAIN TRIGLYCERIDES; GLYCERIN

73647-404-03

ACTIVE INGREDIENT

Camphor ………………………………...…………………………….…. 4%

PURPOSE

Topical Analgesic

Use

Aid for temporary local relief of minor pain in muscles and joints.

WARNINGS

• For external use only. • Ask a doctor before use if you have redness over affected area.

WHEN USING

- Avoid contact with the eyes or mucous membranes.
- Do not apply to wounds or damaged skin.
- Do not apply to the irritated skin or if excessive irritation develops.
- Do not bandage.
- Do not use with heating pad or device.
- Stop use and ask a doctor if condition worsens, or if symptoms persist for more than 7 days, or clear up and occur again within a few days.

PREGNANCY OR BREAST FEEDING

Ask a health professional before use.

KEEP OUT OF REACH OF CHILDREN

If swallowed, get medical help, or contact a Poison Control Center right away.

Directions

Adults and Children over 12 years of age.

● Apply a small amount on the affected area.

● Massage in circular motion, let set for a few seconds.

● Repeat as necessary, but no more than 3 to 4 times daily.

Children under 12 years of age: Do not use, consult a doctor.

Other information

Store tightly closed in a dry place at controlled room temperature between 59°F-86° F (15°C-30° C).

INACTIVE INGREDIENT

Water (Aqua), Alcohol Denat, Ceteareth-25, Glycerin, Caprylic/Capric Triglyceride, Calendula Officinalis Extract, Cannabis Sativa Seed Oil, Carbomer, Sodium Hydroxide, Methyl Salicylate, Benzyl Alcohol, Salicylic Acid, Sorbic Acid, FD&C Yellow No.6 (CI 15985).

Questions or comments?

Contact us +1-833-458-7822